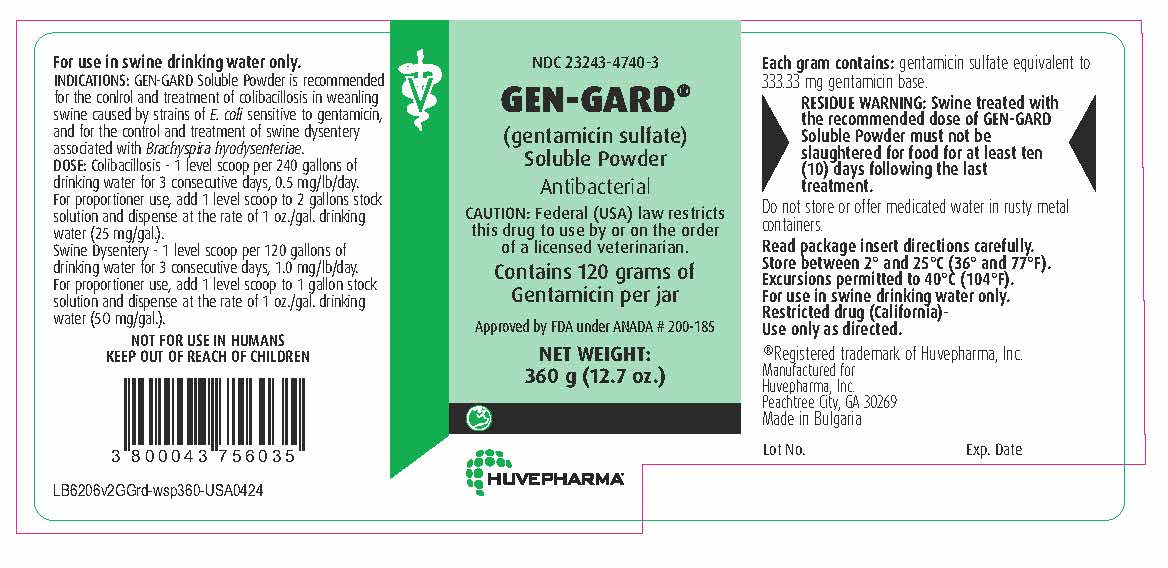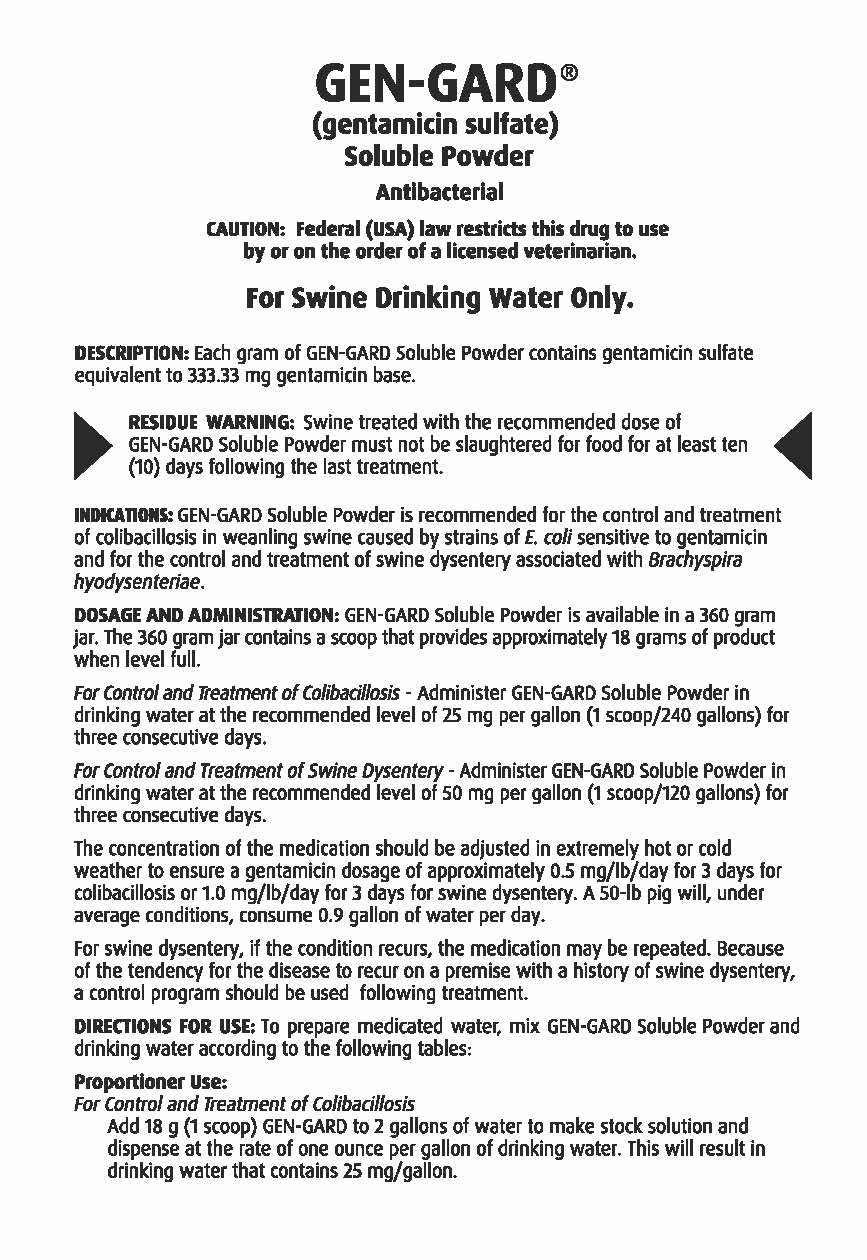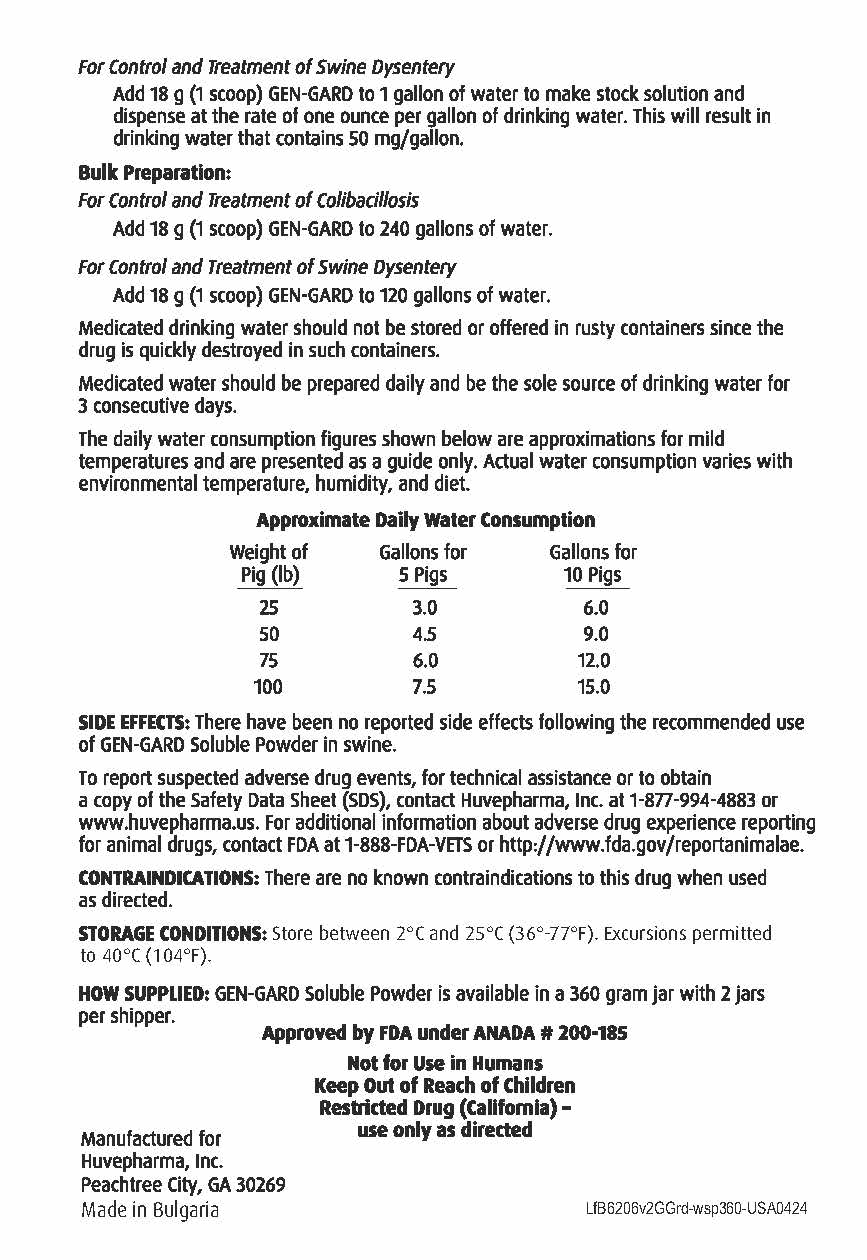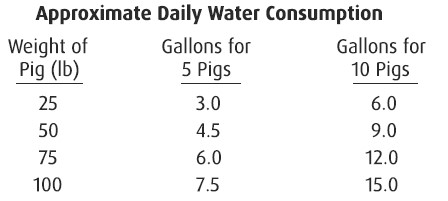 DRUG LABEL: GEN-GARD
NDC: 23243-4740 | Form: POWDER, FOR SOLUTION
Manufacturer: Huvepharma, Inc
Category: animal | Type: PRESCRIPTION ANIMAL DRUG LABEL
Date: 20240604

ACTIVE INGREDIENTS: GENTAMICIN SULFATE 333.33 mg/1 g

NDC 23243-4740-3
GEN-GARD®
(gentamicin sulfate)
Soluble Powder
Antibacterial

GENERAL PRECAUTIONS

CAUTION: Federal (USA) law restricts this drug to use by or on the order
of a licensed veterinarian.

Contains 120 grams of
Gentamicin per jar

Approved by FDA under ANADA # 200-185
NET WEIGHT:
360 g (12.7 oz.)

INDICATIONS AND USAGE

For use in swine drinking water only.
INDICATIONS: GEN-GARD Soluble Powder is recommended for the control and treatment of colibacillosis in weanling
swine caused by strains of E. coli sensitive to gentamicin, and for the control and treatment of swine dysentery
associated with Brachyspira hyodysenteriae.

DOSAGE AND ADMINISTRATION

DOSE: Colibacillosis - 1 level scoop per 240 gallons of drinking water for 3 consecutive days, 0.5 mg/lb/day.
For proportioner use, add 1 level scoop to 2 gallons stock solution and dispense at the rate of 1 oz./gal. drinking
water (25 mg/gal.).
Swine Dysentery - 1 level scoop per 120 gallons of drinking water for 3 consecutive days, 1.0 mg/lb/day.
For proportioner use, add 1 level scoop to 1 gallon stock solution and dispense at the rate of 1 oz./gal. drinking
water (50 mg/gal.).

USER SAFETY WARNINGS

NOT FOR USE IN HUMANS
KEEP OUT OF REACH OF CHILDREN

RESIDUE WARNING

Each gram contains: gentamicin sulfate equivalent to
333.33 mg gentamicin base.

RESIDUE WARNING: Swine treated with the recommended dose of GEN-GARD
Soluble Powder must not be slaughtered for food for at least ten (10) days following
the last treatment.

STORAGE AND HANDLING

Do not store or offer medicated water in rusty metal containers.

Read package insert directions carefully.
Store between 2° and 25°C (36° and 77°F).
Excursions permitted to 40°C (104°F).
For use in swine drinking water only.
Restricted drug (California)-
Use only as directed.

®Registered trademark of Huvepharma, Inc.
Manufactured for
Huvepharma, Inc.
Peachtree City, GA 30269
Made in Bulgaria

Lot No. Exp. Date

GEN-GARD®
(gentamicin sulfate)
Soluble Powder
Antibacterial

GENERAL PRECAUTIONS

CAUTION: Federal (USA) law restricts this drug to use
by or on the order of a licensed veterinarian.

For Swine Drinking Water Only.

RESIDUE WARNING

DESCRIPTION: Each gram of GEN-GARD Soluble Powder contains gentamicin sulfate
equivalent to 333.33 mg gentamicin base.

RESIDUE WARNING: Swine treated with the recommended dose of
GEN-GARD Soluble Powder must not be slaughtered for food for at least ten
(10) days following the last treatment.

INDICATIONS AND USAGE

INDICATIONS: GEN-GARD Soluble Powder is recommended for the control and treatment
of colibacillosis in weanling swine caused by strains of E. coli sensitive to gentamicin
and for the control and treatment of swine dysentery associated with Brachyspira
hyodysenteriae.

DOSAGE AND ADMINISTRATION: GEN-GARD Soluble Powder is available in a 360 gram
jar. The 360 gram jar contains a scoop that provides approximately 18 grams of product
when level full.

For Control and Treatment of Colibacillosis - Administer GEN-GARD Soluble Powder in
drinking water at the recommended level of 25 mg per gallon (1 scoop/240 gallons) for
three consecutive days.

For Control and Treatment of Swine Dysentery - Administer GEN-GARD Soluble Powder in
drinking water at the recommended level of 50 mg per gallon (1 scoop/120 gallons) for
three consecutive days.

The concentration of the medication should be adjusted in extremely hot or cold
weather to ensure a gentamicin dosage of approximately 0.5 mg/lb/day for 3 days for
colibacillosis or 1.0 mg/lb/day for 3 days for swine dysentery. A 50-lb pig will, under
average conditions, consume 0.9 gallon of water per day.

For swine dysentery, if the condition recurs, the medication may be repeated. Because
of the tendency for the disease to recur on a premise with a history of swine dysentery,
a control program should be used following treatment.

INSTRUCTIONS FOR USE

DIRECTIONS FOR USE: To prepare medicated water, mix GEN-GARD Soluble Powder and
drinking water according to the following tables:

Proportioner Use:
For Control and Treatment of Colibacillosis
Add 18 g (1 scoop) GEN-GARD to 2 gallons of water to make stock solution and
dispense at the rate of one ounce per gallon of drinking water. This will result in
drinking water that contains 25 mg/gallon.

For Control and Treatment of Swine Dysentery
Add 18 g (1 scoop) GEN-GARD to 1 gallon of water to make stock solution and
dispense at the rate of one ounce per gallon of drinking water. This will result in
drinking water that contains 50 mg/gallon.

Bulk Preparation:
For Control and Treatment of Colibacillosis
Add 18 g (1 scoop) GEN-GARD to 240 gallons of water.

For Control and Treatment of Swine Dysentery
Add 18 g (1 scoop) GEN-GARD to 120 gallons of water.

Medicated drinking water should not be stored or offered in rusty containers since the
drug is quickly destroyed in such containers.

Medicated water should be prepared daily and be the sole source of drinking water for
3 consecutive days.

The daily water consumption figures shown below are approximations for mild
temperatures and are presented as a guide only. Actual water consumption varies with
environmental temperature, humidity, and diet.

ADVERSE REACTIONS

SIDE EFFECTS: There have been no reported side effects following the recommended use
of GEN-GARD Soluble Powder in swine.

To report suspected adverse drug events, for technical assistance or to obtain
a copy of the Safety Data Sheet (SDS), contact Huvepharma, Inc. at 1-877-994-4883 or
www.huvepharma.us. For additional information about adverse drug experience reporting
for animal drugs, contact FDA at 1-888-FDA-VETS or http://www.fda.gov/reportanimalae.

CONTRAINDICATIONS

CONTRAINDICATIONS: There are no known contraindications to this drug when used
as directed.

STORAGE AND HANDLING

STORAGE CONDITIONS: Store between 2° and 25°C (36° and 77°F). Excursions permitted
to 40°C (104°F).

HOW SUPPLIED: GEN-GARD Soluble Powder is available in a 360 gram jar with 2 jars
per shipper.

Approved by FDA under ANADA # 200-185
Not for Use in Humans
Keep Out of Reach of Children
Restricted Drug (California) –
use only as directed

Manufactured for
Huvepharma, Inc.
Peachtree City, GA 30269
Made in Bulgaria